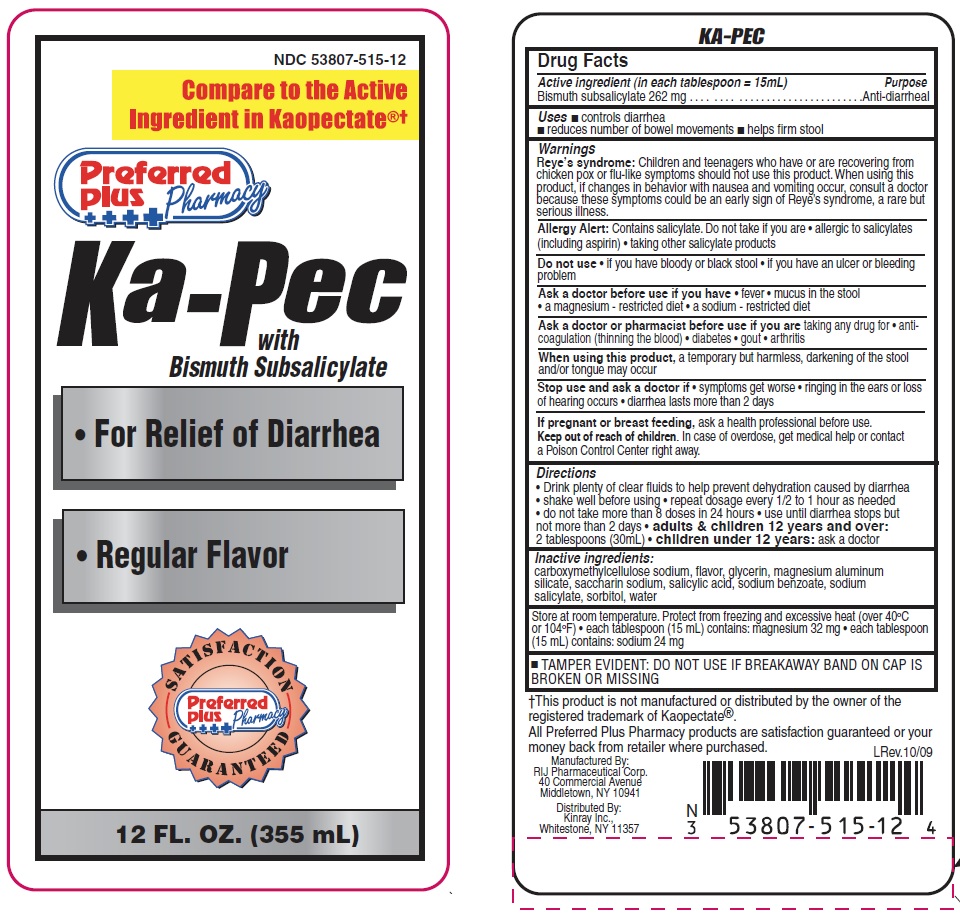 DRUG LABEL: Ka Pec
                
NDC: 53807-515 | Form: LIQUID
Manufacturer: Rij Pharmaceutical Corporation
Category: otc | Type: HUMAN OTC DRUG LABEL
Date: 20180430

ACTIVE INGREDIENTS: BISMUTH SUBSALICYLATE 262 mg/15 mL
INACTIVE INGREDIENTS: CARBOXYMETHYLCELLULOSE SODIUM; GLYCERIN; MAGNESIUM ALUMINUM SILICATE; SACCHARIN SODIUM; SALICYLIC ACID; SODIUM BENZOATE; SODIUM SALICYLATE; SORBITOL; WATER

Drug Facts

Active ingredient (in each tablespoon= 15 mL)

Bismuth subsalicylate 262 mg

Purpose

Anti-diarrheal

Uses

- controls diarrhea
- reduce number of bowel movements
- help firm stool

Warnings

Reye's syndrome: Children and teenagers who have or are recovering from children pox or flu-like symptoms should not use this product. When using this product, if changes in behavior with nausea and vomiting occur, consult a doctor because these symptoms could be an early sign of Reye's syndrome, a rare but serious illness.

Allergy alert: Contains salicylate. Do not take if you are

- allergic to salicylates (including aspirin)
- taking other salicylate products

Do not use

- if you have bloody or black stool
- if you have an ulcer or bleeding problem

Ask a doctor before use if you have

- fever
- mucus in the stool
- a magnesium-restricted diet
- a sodium-restricted diet

Ask a doctor or pharmacist before use if you are

- taking any drug for
- anticoagulation (thinning the blood)
- diabetes
- gout
- arthritis

When using this product

a temporary, but harmless darkening of the stool and/or tongue may occur

Stop use and ask a doctor if

- symptoms get worse
- ringing in the ears or loss of hearing occurs
- diarrhea lasts more than 2 days

If pregnant or breast-feeding,

ask a health professional before use.

Keep out of reach of children.

In case of overdose, get medical help or contact a Poison Control Center right away.

Directions

- Drink plenty of clear fluids to help prevent dehydration caused by diarrhea
- shake well before using
- repeat dosage every 1/2 to 1 hour as needed
- do not take more than 8 doses in 24 hours
- use until diarrhea stops but not more than 2 days
- adults & children 12 years and over: 2 tablespoons (30 mL)
- children under 12 years: ask a doctor

Inactive ingredients

Carboxymethylcellulose sodium, flavor, glycerin, magnesium aluminum silicate, saccharin sodium, salicylic acid, sodium benzoate, sodium saliycylate, sorbitol, water

Other information

- Store at room temperature. Protect from freezing and excessive heat (over 40oC or 104oF)
- each tablespoon (15 mL) contains: magnesium 32 mg
- each tablespoon (15 mL) contains: sodium 24 mg
- TAMPER EVIDENT: DO NOT USE IF BREAKAWAY BAND ON CAP IS BROKEN OR MISSING.